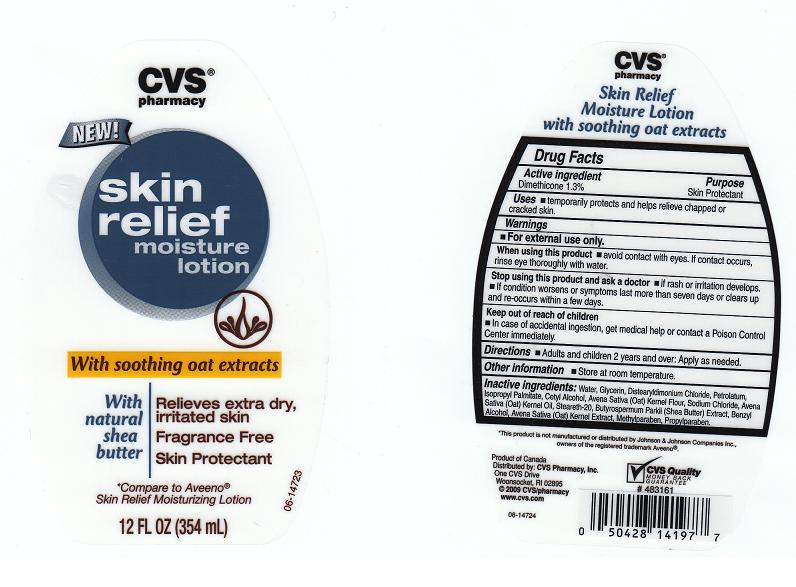 DRUG LABEL: SKIN RELIEF MOISTURE LOT WITH SOOTHING OAT EXTRACTS
NDC: 59779-321 | Form: LIQUID
Manufacturer: CVS PHARMACY
Category: otc | Type: HUMAN OTC DRUG LABEL
Date: 20110117

ACTIVE INGREDIENTS: DIMETHICONE 1.3 mL/100 mL
INACTIVE INGREDIENTS: WATER; GLYCERIN; DISTEARYLDIMONIUM CHLORIDE; PETROLATUM; ISOPROPYL PALMITATE; CETYL ALCOHOL; OATMEAL; SODIUM CHLORIDE; OAT KERNEL OIL; STEARETH-20; SHEANUT OIL; BENZYL ALCOHOL; OAT; METHYLPARABEN; PROPYLPARABEN

DRUG FACTS

ACTIVE INGREDIENT

DIMETHICONE 1.3 PERCENT

PURPOSE

SKIN PROTECTANT

USES

TEMPORARILY PROTECTS AND HELPS RELIEVE CHAPPED OR CRACKED SKIN.

WARNINGS

FOR EXTERNAL USE ONLY.

WHEN USING THIS PRODUCT

AVOID CONTACT WITH EYES. IF CONTACT OCCURS, RINSE EYE THOROUGHLY WITH WATER.

STOP USING THIS PRODUCT AND ASK A DOCTOR

IF RASH OR IRRITATION DEVELOPS. IF CONDITION WORSENS OR SYMPTOMS LAST MORE THAN SEVEN DAYS OR CLEARS UP AND RE-OCCURS WITHIN A FEW DAYS.

KEEP OUT OF REACH OF CHILDREN

IN CASE OF ACCIDENTAL INGESTION, GET MEDICAL HELP OR CONTACT A POISON CONTROL CENTER IMMEDIATELY.

DIRECTIONS

ADULTS AND CHILDREN 2 YEARS AND OVER: APPLY AS NEEDED.

OTHER INFORMATION

STORE AT ROOM TEMPERATURE.

INACTIVE INGREDIENTS

WATER, GLYCERIN, DISTEARYLDIMONIUM CHLORIDE, PETROLATUM, ISOPROPYL PALMITATE, CETYL ALCOHOL, AVENA SATIVA (OAT) KERNEL FLOUR, SODIUM CHLORIDE, AVENA SATIVA (OAT) KERNEL OIL, STEARETH-20, BUTYROSPERMUM PARKII (SHEA BUTTER) EXTRACT, BENZYL ALCOHOL, AVENA SATIVA (OAT) KERNEL EXTRACT, METHYLPARABEN, PROPYLPARABEN.